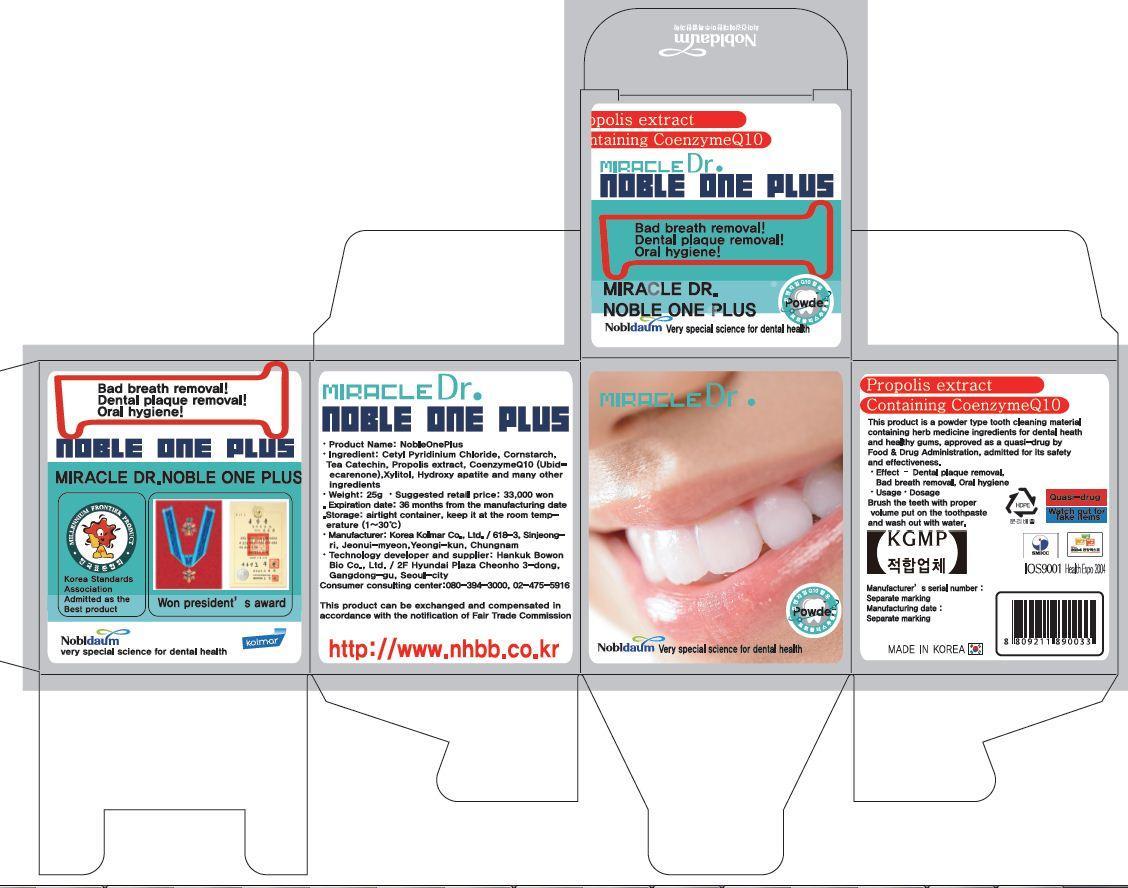 DRUG LABEL: Noble 1 Plus
NDC: 60319-4001 | Form: POWDER, DENTIFRICE
Manufacturer: Hankuk Bowonbio Co., Ltd
Category: otc | Type: HUMAN OTC DRUG LABEL
Date: 20191204

ACTIVE INGREDIENTS: XYLITOL 0.7 g/100 g
INACTIVE INGREDIENTS: CETYLPYRIDINIUM CHLORIDE; LACTOSE MONOHYDRATE; STARCH, CORN; SORBITOL; UBIDECARENONE; LICORICE; TRIBASIC CALCIUM PHOSPHATE; PROPOLIS WAX

Drug Facts

active ingredient: xylitol<text><contentstyleCode="xmChange"></content></text>

INACTIVE INGREDIENT

cetylpyridinium chloride, lactose monohydrate, corn starch, d-sorbitol, ubidecarenone, glycyrrhizae extract, tea chatechin, hydroxyapatite, propolis extract, menthol powder, spirulina color<text><contentstyleCode="xmChange"></content></text>

PURPOSE

whiten and strong teeth
removal of bad breath
prevention of gingivitis and periodontitis
prevention of periodontal diseases and gum diseases
removal of dental plaque<text><contentstyleCode="xmChange"></content></text>

KEEP OUT OF REACH OF CHILDREN

keep out of reach of the children<text><contentstyleCode="xmChange"></content></text>

INDICATIONS AND USAGE

apply Proper Amount of the toothpaste on the tooth.<text><contentstyleCode="xmChange"></content></text>

WARNINGS

■ For tooth only.
■ Avoid contact with eyes.
■ Do not swallow. If swallowed, get medical help.
<text><contentstyleCode="xmChange"></content></text>

DOSAGE AND ADMINISTRATION

brush your teeth by putting appropriate amount of powder
<text><contentstyleCode="xmChange"></content></text>

RECENT MAJOR CHANGES

<text><contentstyleCode="xmChange"></content></text>

PACKAGE LABEL

<text><contentstyleCode="xmChange"></content></text>